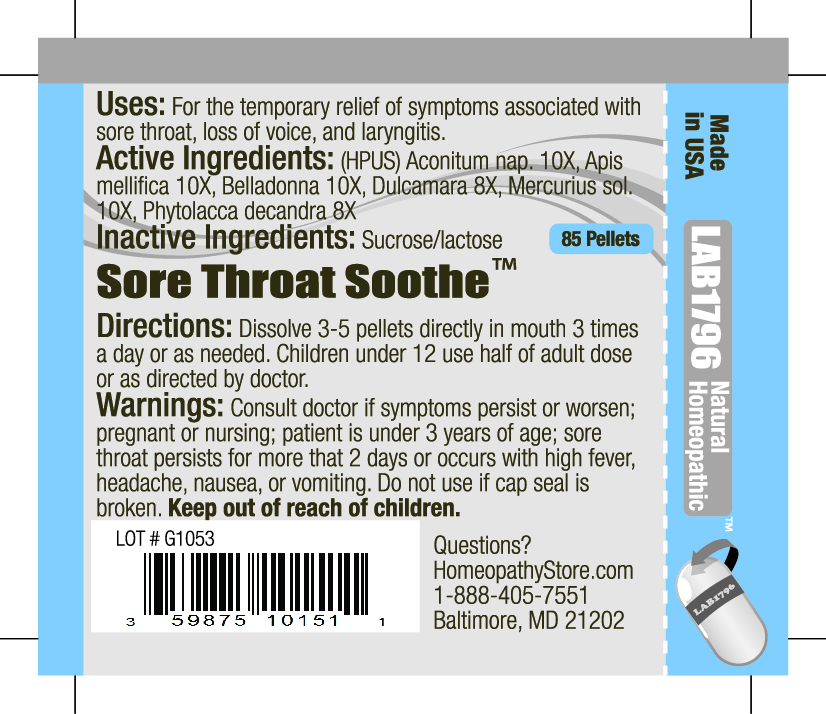 DRUG LABEL: Lab1796 Sore Throat Soothe
NDC: 59875-1015 | Form: PELLET
Manufacturer: HomeopathyStore.com
Category: homeopathic | Type: HUMAN OTC DRUG LABEL
Date: 20101229

ACTIVE INGREDIENTS: ACONITUM NAPELLUS 10 [hp_X]/1 1; APIS MELLIFERA 10 [hp_X]/1 1; ATROPA BELLADONNA 10 [hp_X]/1 1; SOLANUM DULCAMARA TOP 8 [hp_X]/1 1; MERCURIUS SOLUBILIS 10 [hp_X]/1 1; PHYTOLACCA AMERICANA ROOT 8 [hp_X]/1 1
INACTIVE INGREDIENTS: SUCROSE; LACTOSE

Sore Throat Soothe

Uses:

For the temporary relief of symptoms associated with sore throat, loss of voice, and laryngitis.

Active Ingredients:

(HPUS) Aconitum nap. 10X, Apis mellifica 10X, Belladonna 10X, Dulcamara 8X , Mercurius sol. 10X, Phytolacca decandra 8X

Inactive Ingredients:

Sucrose/lactose

Directions:

DOSAGE AND ADMINISTRATION

Dissolve 3-5 pellets directly in mouth 3 times a day or as needed. Children under 12 use half of adult dose or as directed by doctor.

Warnings:

Consult doctor if symptoms persist or worsen; pregnant or nursing; patient is under 3 years of age; sore throat persists for more than 2 days or occurs with high fever, headache, nausea, or vomiting. Do not use if cap seal is broken.

Keep out of reach of children.